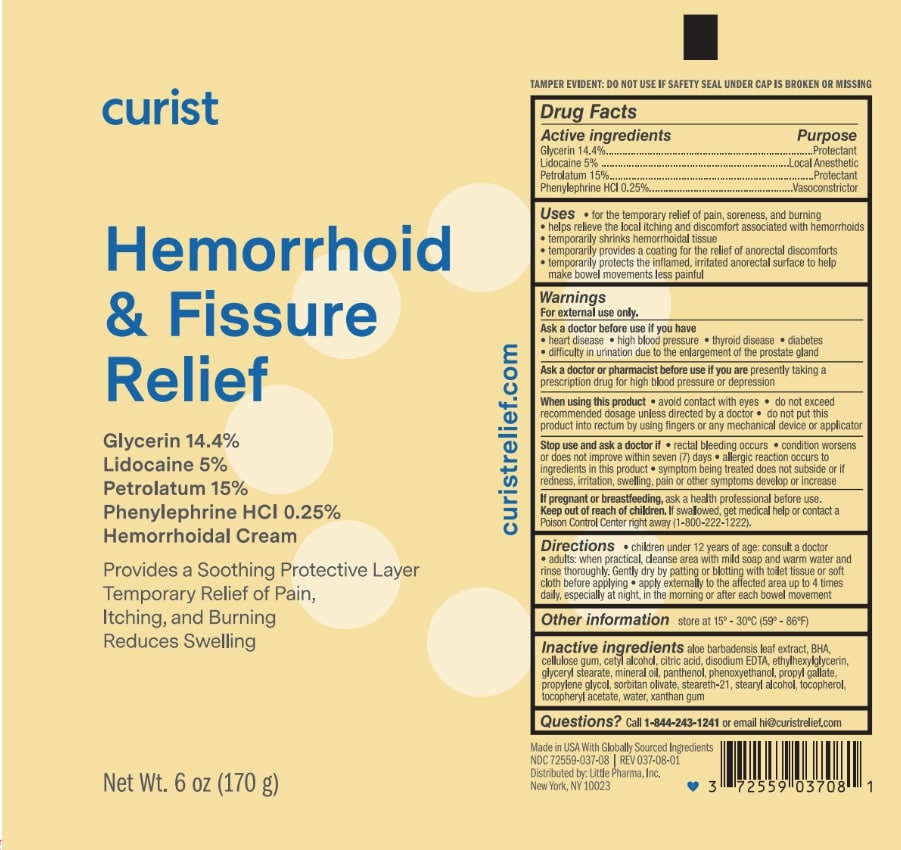 DRUG LABEL: Curist Hemorrhoid Fissure Relief
NDC: 72559-037 | Form: CREAM
Manufacturer: Little Pharma, Inc
Category: otc | Type: HUMAN OTC DRUG LABEL
Date: 20250306

ACTIVE INGREDIENTS: PETROLATUM 15 g/100 g; LIDOCAINE 5 g/100 g; GLYCERIN 14.4 g/100 g; PHENYLEPHRINE HYDROCHLORIDE 0.25 g/100 g
INACTIVE INGREDIENTS: EDETATE DISODIUM; MINERAL OIL; BHA; WATER; CITRIC ACID; PHENOXYETHANOL; STEARYL ALCOHOL; CELLULOSE GUM; ALOE BARBADENSIS LEAF; ETHYLHEXYLGLYCERIN; GLYCERYL STEARATE; PROPYLENE GLYCOL; PROPYL GALLATE; SORBITAN OLIVATE; STEARETH-21; TOCOPHEROL; CETYL ALCOHOL; ALPHA-TOCOPHEROL ACETATE; XANTHAN GUM; PANTHENOL

Active Ingredients

Glycerin 14.4%

Lidocaine 5%

Petrolatum 15%

Phenylephrine HCL 0.25%

Purpose

Hemorrhoidal Cream

Warnings

For external use only

Uses

- for the temporary reliedf of pain, soreness and burning
- helps relieve the local itching and discomfort associated with hemorrhoids
- temporarily shrinks hemorrhoidal tissue
- temporarily provides a coating for the relief of anorectal discomforts
- temporarily protects the inflamedm irritated abirectak syrface to help make bowel movements less painful

Ask a doctor before use if you have

- heart disease
- high blood pressure
- thyroid disease
- diabetes
- difficult in urination due to the enlargement of the prostate gland

Ask a doctor or pharmacist before use if you are presently taking a prescripton drug for high blood preassure or depression

When using this product

- avoid contact with eyes
- do not exceed recommended dosage unless directed by a doctor
- do not put his product into rectum by using fingers or any mechanical device or applicator

PREGNANCY OR BREAST FEEDING

If pregnant or breastfeeding, ask a health professional before use.

Stop use and ask a doctor if

- rectal bleeding occurs
- condition worsens or does not imporve within seven (7) days
- allergic reaction occurs to ingredients in this product
- symptom being treated does not subside or if redness, irritation, swelling, pain or thor symptons develop or increase

Keep out of reach of children.

OTHER SAFETY INFORMATION

If swallowed, get medical help or contact a Poison Control Center right sway (1-800-222-1222)

Directions

- children under 12 years of age: consult a doctor
- adults: when practical, cleanse area with mild soap and warm water and rinse thoroughly. Gently dry by patting or blotting with toilet tissue or soft cloth before applying
- apply externally to the affected area up to 4 times daily, especially at night, in the moring or after each bowel movement

Other information

store at 15° - 30°C (59°-86°F)

Inactive Ingredients

aloe barbadensis leaf extract, BHA, cellulose gum, cetyl alcohol, citric acid, disodium EDTA, ethylhexylglycerin, glyceryl stearate, mineral oil, panthenol, phenoxyethanol, propyl gallate, propylene glycol, sorbitan olivate, steareth-21, stearyl alcohol, tocopherol, tocopheryl acetate, water, zanthan gum

QUESTIONS

Questions? Call 1-844-243-1241 or email hi@curistrelief.com

Made in USA With Globally Sourced Ingedients

NDC 72559-037-08

REV 037-08-01

Distributed by: Little Pharma, Inc.

New York, NY 10023

PACKAGE LABEL

curist

Hemorrhoid & Fissure Relief

Glycerin 14.%

Lidocaine 5%

Petrolatum 15%

Phenylephrine HCL 0.25%

Hemorrhoidal Cream

Provides a Soothing Protective Layer

Temporary Relief of Pain,

Itching, adn Burning

Reduces Swelling

Net Wt. 6 oz (170g)